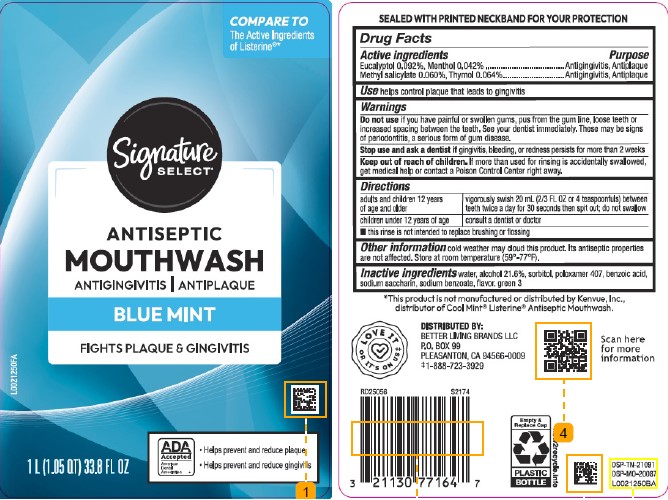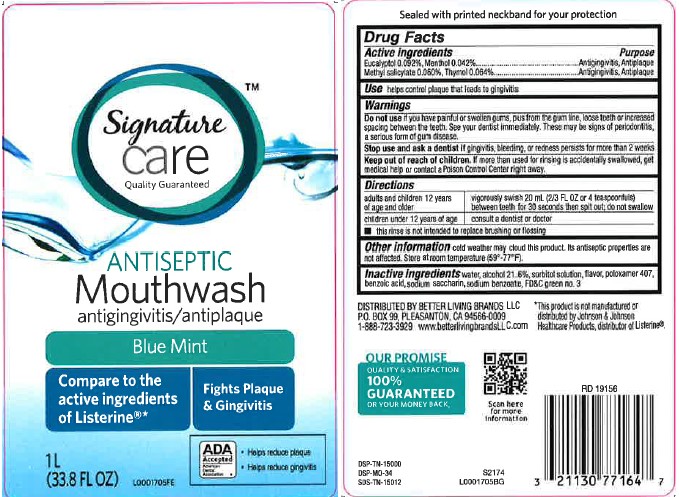 DRUG LABEL: Antispetic
NDC: 21130-664 | Form: MOUTHWASH
Manufacturer: Better Living Brands, LLC
Category: otc | Type: HUMAN OTC DRUG LABEL
Date: 20260224

ACTIVE INGREDIENTS: EUCALYPTOL 0.92 mg/1 mL; MENTHOL 0.42 mg/1 mL; METHYL SALICYLATE 0.6 mg/1 mL; THYMOL 0.64 mg/1 mL
INACTIVE INGREDIENTS: WATER; ALCOHOL; SORBITOL; POLOXAMER 407; BENZOIC ACID; SACCHARIN SODIUM; SODIUM BENZOATE; FD&C GREEN NO. 3

Signature Care_Signature Select 664.003/664AT-AU
Blue Mint Antiseptic Mouthrinse

TEP

Sealed with printed neckband for your protection

Active ingredients

Eucalyptol 0.092%

Menthol 0.042%

Methyl salicylate 0.060%

Thymol 0.064%

Purpose

Antigingivitis, Antiplaque

Use

helps control plaque that leads to gingivitis

Warnings

For this product

Do not use

If you have painful or swollen gums, pus from the gum line, loose teeth or increased spacing between the teeth. See your dentist immediately. These may be signs of periodontitis, a serious form of gum disease.

Stop use and ask a dentist if

gingivitis, bleeding, or redness persists for more than 2 weeks.

Keep out of reach of children.

If more than used for rinsing is accidentally swallowed, get medical help or contact a Poison Control Center right away.

Directions

adults and children 12 years of age and older - vigorously swish 20 mL (2/3 FL OZ or 4 teaspoonfuls) between teeth twice a day for 30 seconds then spit out; do not swallow

children under 12 years of age - consult a dentist or doctor

- this rinse is not intended to replace brushing or flossing

Other information

Cold weather may cloud this product. Its antiseptic properties are not affected. Store at room temperature (59⁰-77⁰F)

Inactive ingredients

water, alcohol 21.6%, sorbitol, poloxamer 407, benzoic acid, sodium saccharin, sodium benzoate, flavor, green 3

Disclaimer

*This product is not manufactured or distributed by Kenvue, Inc., distributor of Cool Mint®Listerine®Antiseptic Mouthwash.

Adverse Reactions

DISTRIBUTED BY:

BETTER LIVING BRANDS LLC

P.O. BOX 99

PLEASANTON, CA 94566-0009

‡1-888-723-3929

LOVE IT OR IT'S ON US

Scan here for more information

Empty & Replace Cap

PLASTIC BOTTLE

how2recycle.com

DSP-TN-21091

DSP-MO-20087

principal display panel

Signature

CARE™

Quality Guaranteed

ANTISEPTIC

Mouthwash

antigingivitis/antiplaque

Blue Mint

Compare to the active ingredients of Listerine*

Fights Plaque & Gingivitis

ADA Accepted

American Dental Association

- Helps reduce plaque
- Helps reduce gingivitis

1 L

(33.8 FL OZ)

PRINCIPAL DISPLAY PANEL

COMPARE TO

The Active Ingredients of Listerine®*

Signature

SELECT®

ANTISEPTIC

MOUTHWASH

ANTIGINGIVITIS/ANTIPLAQUE

BLUE MINT

FIGHTS PLAQUE & GINGIVITIS

ADA Accepted

American Dental Association

- Helps prevent and reduce plaque
- Helps prevent and reduce gingivitis

1 L (1.05 QT) 33.8 FL OZ